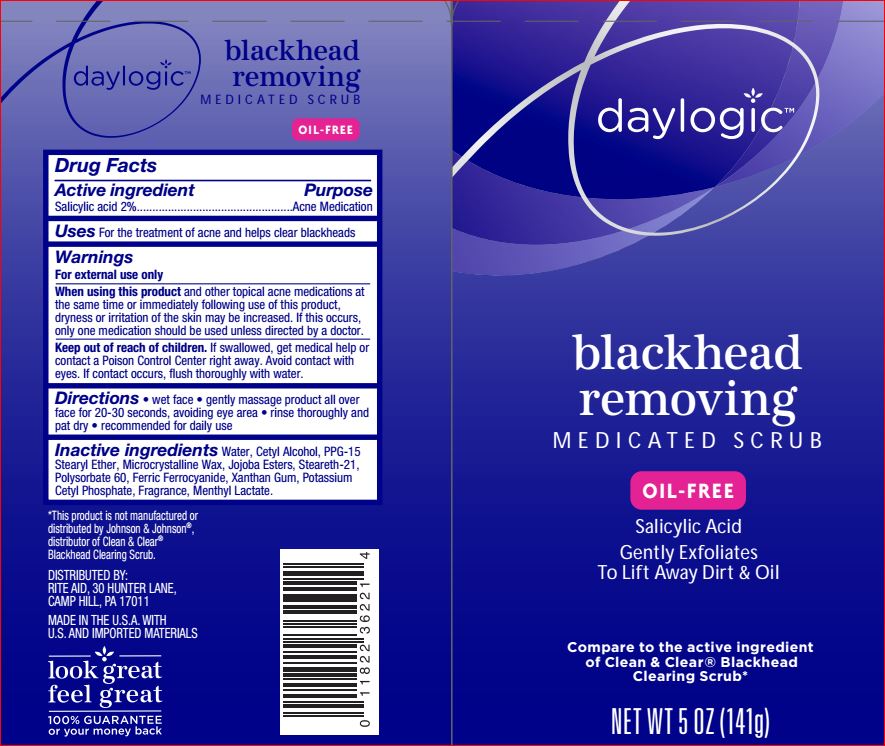 DRUG LABEL: Bleackhead removing Medicated scrub
NDC: 11822-7798 | Form: LOTION
Manufacturer: Rite Aid
Category: otc | Type: HUMAN OTC DRUG LABEL
Date: 20180522

ACTIVE INGREDIENTS: Salicylic Acid 2 g/100 g
INACTIVE INGREDIENTS: Water; Cetyl Alcohol; PPG-15 Stearyl Ether; Microcrystalline Wax; HYDROGENATED JOJOBA OIL, RANDOMIZED; Steareth-21; Polysorbate 60; Ferric Ferrocyanide; Xanthan Gum; Potassium Cetyl Phosphate; MENTHYL LACTATE, (-)-

Active ingredient Purpose
Salicylic acid 2%..................................................Acne Medication

INDICATIONS AND USAGE

Uses For the treatment of acne and helps clear blackheads

Warnings
For external use only
When using this product and other topical acne medications at
the same time or immediately following use of this product,
dryness or irritation of the skin may be increased. If this occurs,
only one medication should be used unless directed by a doctor

Keep out of reach of children. If swallowed, get medical help or contact a Poison Control Center right away. Avoid contact with
eyes. If contact occurs, flush thoroughly with water.

DOSAGE AND ADMINISTRATION

Directions • wet face • gently massage product all over face for 20-30 seconds, avoiding eye area • rinse thoroughly and
pat dry • recommended for daily use

Inactive ingredients

Water, Cetyl Alcohol, PPG-15
Stearyl Ether, Microcrystalline Wax, Jojoba Esters, Steareth-21,
Polysorbate 60, Ferric Ferrocyanide, Xanthan Gum, Potassium
Cetyl Phosphate, Fragrance, Menthyl Lactate.